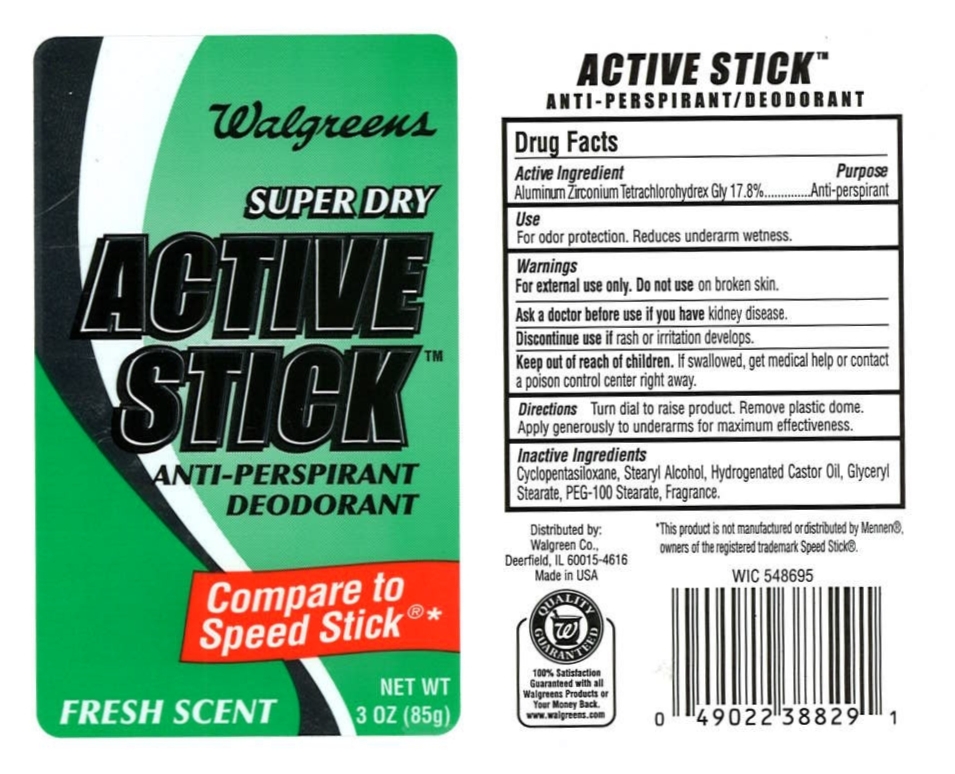 DRUG LABEL: Walgreens Active Stick
NDC: 10889-106 | Form: STICK
Manufacturer: VVF Kansas Services LLC
Category: otc | Type: HUMAN OTC DRUG LABEL
Date: 20091023

ACTIVE INGREDIENTS: aluminum zirconium tetrachlorohydrex gly 17.8 1/1 1

Walgreens Active Stick (Aluminun Zirconium Tetrachlorohydrex Gly)

ACTIVE INGREDIENT

Aluminum Zirconium Tetrachlorohydrex Gly 17.8%

PURPOSE

Anti-perspirant

USES

For odor protection. Reduces underarm wetness.

Turn dial to raise product. Remove plastic dome. Apply a thin even layer to underarms for maximum effectiveness. Do not over apply.

WARNINGS

For external use only. Do not use on broken skin.

Ask a doctor before you use if you have kidney disease.

Discontinue use if rash or irritation develops.

Keep out of reach of children. If swallowed, get medical help or contact a poison control center right away.

INACTIVE INGREDIENTS

Cyclopentasiloxane, Stearyl Alcohol, Hydrogenated Castor Oil, Glyceryl Stearate, PEG-100 Stearate, Fragrance

* This product is not manufactured or distributed by Mennen(R), owners of the registered trademark Speed Stick (R).
Distributed by:
Walgreen Co.,
Deerfield, IL 60015-4616
100% Satisfaction Guaranteed www.walgreens.com
Made in USA
WIC 548695

PRODUCT LABEL

Walgreens

SUPER DRY

ACTIVE STICK(TM)

Anti-Perspirant Deodorant

Compare to Speed Stick*

Fresh Scent

NET WT. 3 OZ. (85g)